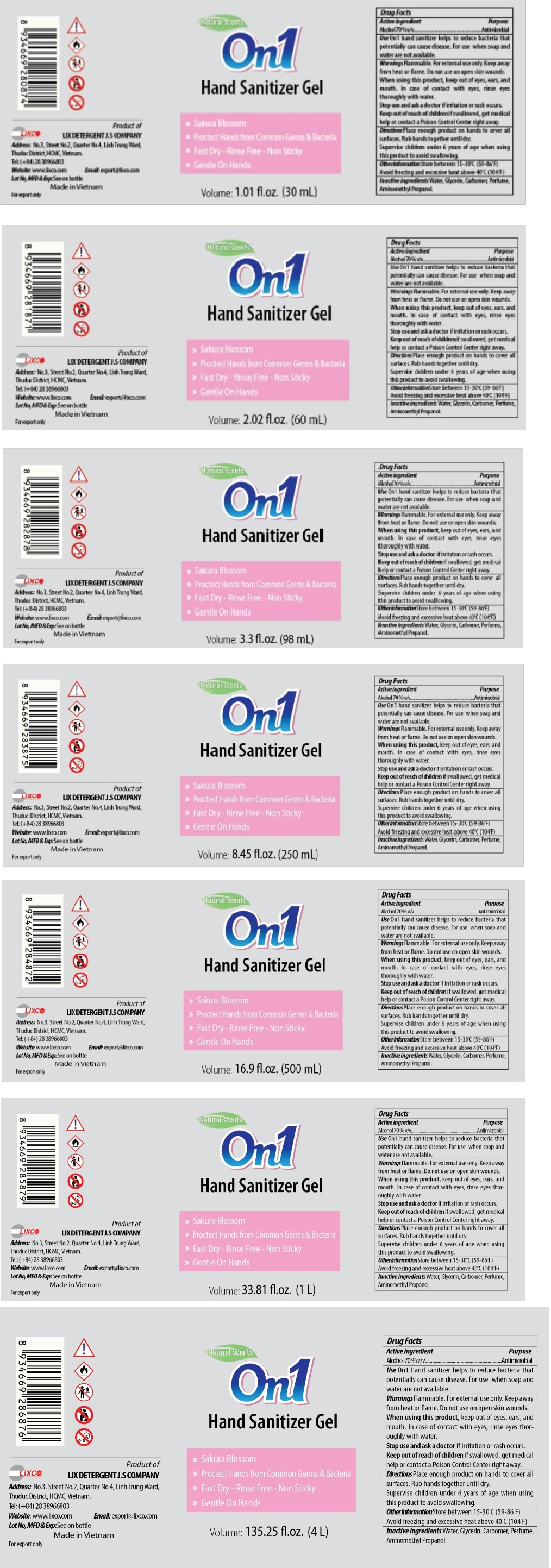 DRUG LABEL: ON1 Hand Sanitizer
NDC: 76802-102 | Form: GEL
Manufacturer: LIX DETERGENT JOINT STOCK COMPANY
Category: otc | Type: HUMAN OTC DRUG LABEL
Date: 20200601

ACTIVE INGREDIENTS: ALCOHOL 70 mL/100 mL
INACTIVE INGREDIENTS: WATER; GLYCERIN; CARBOMER INTERPOLYMER TYPE A (ALLYL SUCROSE CROSSLINKED); AMINOMETHYLPROPANOL

On1 Hand Sanitizer Gel

Active ingredient

Alcohol 70% v/v

Purpose

Antimicrobial

INDICATIONS AND USAGE

Use On1 hand sanitizer helps to reduce bacteria that potentially can cause disease. For use when soap and water are not available.

WARNINGS

Warnings Flammable. For external use only. Keep away from heat or flame. Do not use on open skin wounds.

When using this product, keep out of eyes, ears, and mouth. In case of contact with eyes, rinse eyes thoroughly with water.

Stop use and ask a doctor if irritation or rash occurs.

Keep out of reach of children If swallowed, get medical help or contact a Poison Control Center right away.

DOSAGE AND ADMINISTRATION

Directions Place enough product on hands to cover all surfaces. Rub hands together until dry.
Supervise children under 6 years of age when using this product to avoid swallowing.

Other information Store between 15-30°C (59-86°F)
Avoid freezing and excessive heat above 40°C (104°F)

INACTIVE INGREDIENT

Inactive ingredients Water, Glycerin, Carbomer, Perfume, Aminomethyl Propanol

Natural scents

>> Sakura Blossom

>> Protect Hands from Common Germs & Bacteria

>> Fast Dry - Rinse Free - Non Sticky

>> Gentle On Hands

Product of

LIX DETERGENT J.S COMPANY

Address: No.3, Street No.2, Quarter No.4, Linh Trung Ward,

Thuduc District, HCMC, Vietnam.

Tel: (+84) 28 38966803

Website: www.lixco.com Email:export@lixco.com

Made in Vietnam

For export only